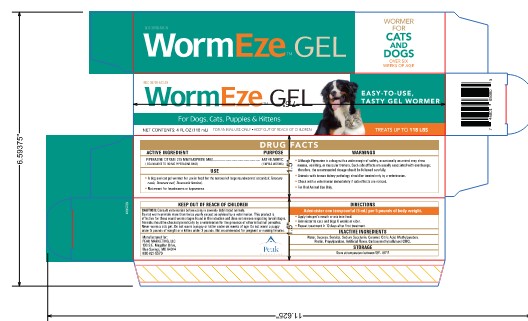 DRUG LABEL: WormEze Gel for Dogs, Cats, Puppies and Kittens
NDC: 30798-543 | Form: GEL
Manufacturer: Durvet Inc.
Category: animal | Type: OTC ANIMAL DRUG LABEL
Date: 20260114

ACTIVE INGREDIENTS: PIPERAZINE CITRATE 118 mg/118 mL
INACTIVE INGREDIENTS: CARAMEL; CITRIC ACID MONOHYDRATE; METHYLPARABEN; SACCHARIN SODIUM; SORBITOL; SUCROSE; WATER; PROPYLPARABEN; CARBOXYMETHYLCELLULOSE; PECTIN

WormEze Gel Wormer for Cats and Dogs

Active Ingredient

Piperazine Citrate 275 mg/teaspoon (5ml)
(Equivalent to 110 mg Piperazine Base)

Purpose

Anthelmintic
(Expels Worms)

Uses:

A dog and cat gel wormer for use in food for the removal of large roundworms (ascarids) (Toxocara canis, Toxocara cati, Toxascaris leonina).

Not meant for heartworms or tapeworms.

Warnings:

- Although Piperazine is a drug with a wide margin of safety, occasionally an animal may show nausea, vomiting, or muscular tremors. Such side effects are usually associated with overdosage; therefore, the recommended dosage should be followed carefully.
- Animals with known kidney pathology should be treated only by a veterinarian.
- Check with a veterinarian immediately if side effects are noticed.
- For oral animal use only.

KEEP OUT OF REACH OF CHILDREN

Keep this and all pet products out of reach of children.

Caution:

Consult veterinarian before using in severely debilitated animals.

Do not worm animals more than twice yearly except as advised by a veterinarian. This product is effective for those round worm stages found in the intestine and does not remove migrating larval stages. Animals should be checked periodically by a veterinarian for the presence of other intestinal parasites.

Never worm a sick pet. Do not worm a puppy or kitten under six weeks of age.

Do not worm a puppy under 5 pounds of weight or a kitten under 3 pounds.

Not recommended for pregnant or nursing females.

Directions:

Administer one teaspoonful (5 mL) per 5 pounds of body weight.

- Apply into pet's mouth or mix into food.
- Administer to cats and dogs 6 weeks or older.
- Repeat treatment in 10 days after first treatment.

Storage:

Store at temperature between 59-86o F.

Inactive Ingredients:

Water, Sucrose, Sorbitol, Sodium Saccharin, Caramel, Citric Acid, Methylparaben, Pectin, Propylparaben, Artificial Flavor, Carboxymethylcellulose (CMC).

Packaging

EASY-TO-USE TASTY GEL WORMER

FOR THE REMOVAL OF
TOXOCARA CATI
TOXASCARIS LEONINA

EFFECTIVE IN DOGS, CATS, PUPPIES AND KITTENS

Manufactured For:
Peak Marketing, LLC
100 S.E. Magellan Drive,
Blue Springs, MO 64014
800-821-5570